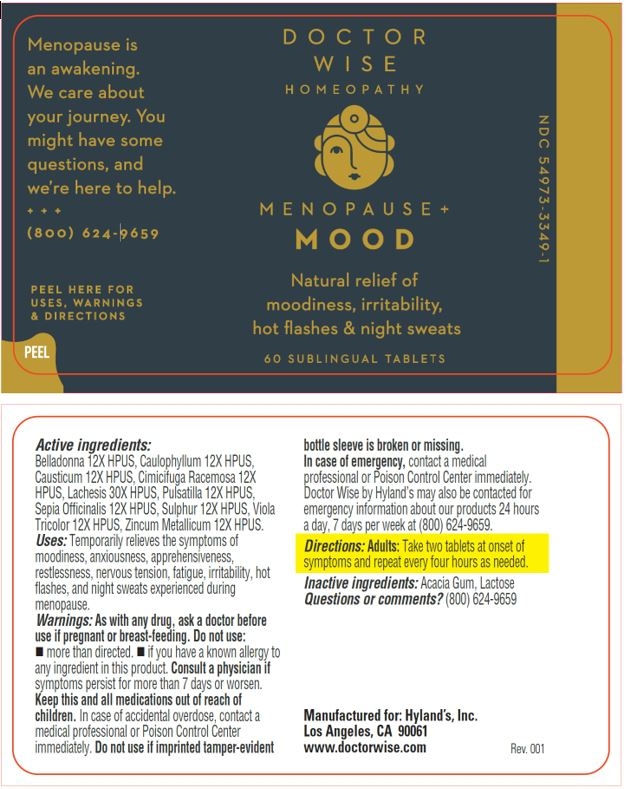 DRUG LABEL: Menopause Plus Mood
NDC: 54973-3349 | Form: TABLET
Manufacturer: Hyland's Inc.
Category: homeopathic | Type: HUMAN OTC DRUG LABEL
Date: 20221212

ACTIVE INGREDIENTS: SULFUR 12 [hp_X]/1 1; ATROPA BELLADONNA 12 [hp_X]/1 1; CAULOPHYLLUM THALICTROIDES ROOT 12 [hp_X]/1 1; CAUSTICUM 12 [hp_X]/1 1; BLACK COHOSH 12 [hp_X]/1 1; ANEMONE PULSATILLA 12 [hp_X]/1 1; SEPIA OFFICINALIS JUICE 12 [hp_X]/1 1; VIOLA TRICOLOR 12 [hp_X]/1 1; ZINC 12 [hp_X]/1 1; LACHESIS MUTA VENOM 30 [hp_X]/1 1
INACTIVE INGREDIENTS: ACACIA; LACTOSE MONOHYDRATE

Doctor Wise Menopause+ Mood

Active ingredients

Belladonna 12X HPUS, Caulophyllum 12X HPUS, Causticum 12X HPUS, Cimicifuga Racemosa 12X HPUS, Lachesis 30X HPUS, Pulsatilla 12X HPUS, Sepia Officinalis 12X HPUS, Sulphur 12X HPUS, Viola Tricolor 12X HPUS, Zincum Metallicum 12X HPUS.

Uses

PURPOSE

Temporarily relieves the symptoms of moodiness, anxiousness, apprehensiveness, restlessness, nervous tension, fatigue, irritability, hot flashes, and night sweats experienced during menopause.

Warnings

PREGNANCY OR BREAST FEEDING

As with any drug, ask a doctor before use if pregnant or breast-feeding.

Do not use: • more than directed.  • if you have a known allergy to any ingredient in this product.

ASK DOCTOR

Consult a physician if symptoms persist for more than 7 days or worsen.

KEEP OUT OF REACH OF CHILDREN

Keep this and all medications out of reach of children. In case of accidental overdose, contact a medical professional or Poison Control Center immediately.

Do not use if imprinted tamper-evident bottle sleeve is broken or missing.

In case of emergency, contact a medical professional or Poison Control Center immediately. Doctor Wise by Hyland’s may also be contacted for emergency information about our products 24 hours a day, 7 days per week at (800) 624-9659.

Directions

Adults: Take two tablets at onset of symptoms and repeat every four hours as needed.

Inactive ingredients

Acacia Gum, Lactose

Questions or comments?

(800) 624-9659

Principal Display Panel - 60 Sublingual Tablet Bottle Label

DOCTOR

WISE

HOMEOPATHY

MENOPAUSE+

MOOD

Natural relief of

moodiness, irritability,

hot flashes & night sweats

60 SUBLINGUAL TABLETS